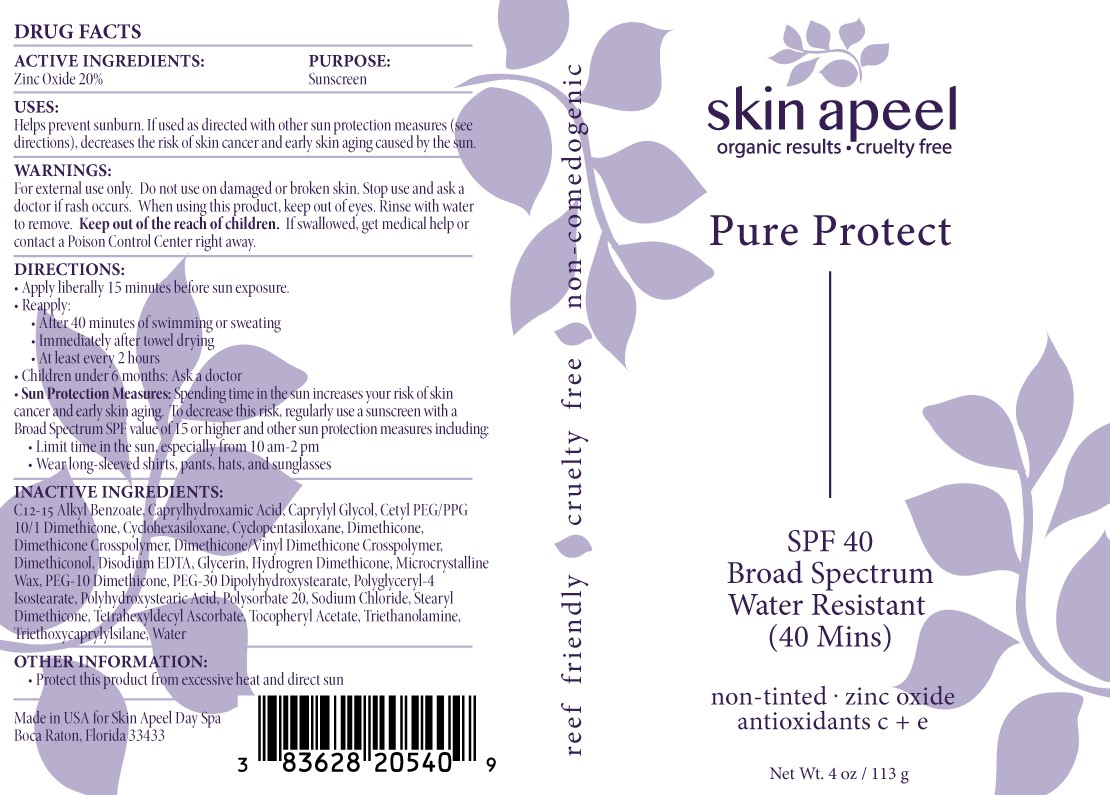 DRUG LABEL: Skin Apeel Pure Protect SPF 40 Broad Spectrum
NDC: 83628-205 | Form: CREAM
Manufacturer: Skin Apeel, Inc.
Category: otc | Type: HUMAN OTC DRUG LABEL
Date: 20251208

ACTIVE INGREDIENTS: ZINC OXIDE 200 mg/1 g
INACTIVE INGREDIENTS: DIMETHICONE/VINYL DIMETHICONE CROSSPOLYMER (SOFT PARTICLE); CAPRYLHYDROXAMIC ACID; CYCLOMETHICONE 6; GLYCERIN; PEG-10 DIMETHICONE (600 CST); TETRAHEXYLDECYL ASCORBATE; TROLAMINE; CAPRYLYL GLYCOL; POLYSORBATE 20; ALKYL (C12-15) BENZOATE; CETYL PEG/PPG-10/1 DIMETHICONE (HLB 5); DIMETHICONE CROSSPOLYMER (450000 MPA.S AT 12% IN CYCLOPENTASILOXANE); EDETATE DISODIUM; DIMETHICONOL (2000 CST); MICROCRYSTALLINE WAX; POLYGLYCERYL-4 ISOSTEARATE; POLYHYDROXYSTEARIC ACID (2300 MW); .ALPHA.-TOCOPHEROL ACETATE; WATER; DIMETHICONE 100; PEG-30 DIPOLYHYDROXYSTEARATE (4000 MW); HYDROGEN DIMETHICONE (20 CST); CYCLOMETHICONE 5; STEARYL DIMETHICONE (400 MPA.S AT 50C); SODIUM CHLORIDE; TRIETHOXYCAPRYLYLSILANE

ACTIVE INGREDIENTS:Zinc Oxide 20%

PURPOSE:Sunscreen

USES: Helps prevent sunburn. If used as directed with other sun protection measures (see directions), decreases the risk of skin cancer and early skin aging caused by the sun.

DIRECTIONS:

• Apply liberally 15 minutes before sun exposure.

• Reapply:

• After 40 minutes of swimming or sweating

• Immediately after towel drying

• At least every 2 hours

• Children under 6 months: Ask a doctor

• Sun Protection Measures: Spending time in the sun increases your risk of skin cancer and early skin aging. To decrease this risk, regularly use a sunscreen with a Broad Spectrum SPF value of 15 or higher and other sun protection measures including:

• Limit time in the sun, especially from 10 am-2 pm

• Wear long-sleeved shirts, pants, hats, and sunglasses

INACTIVE INGREDIENT

INACTIVE INGREDIENTS: C- Alkyl Benzoate, Caprylhydroxamic Acid, Caprylyl Glycol, Cetyl PEG/PPG 10/1 Dimethicone, Cyclohexasiloxane, Cyclopentasiloxane, Dimethicone, Dimethicone Crosspolymer, Dimethicone/Vinyl Dimethicone Crosspolymer, Dimethiconol, Disodium EDTA, Glycerin, Hydrogren Dimethicone, Microcrystalline Wax, PEG-10 Dimethicone, PEG-30 Dipolyhydroxystearate, Polyglyceryl-4 Isostearate, Polyhydroxystearic Acid, Polysorbate 20, Sodium Chloride, Stearyl Dimethicone, Tetrahexyldecyl Ascorbate, Tocopheryl Acetate, Triethanolamine, Triethoxycaprylylsilane, Water

OTHER INFORMATION: • Protect this product from excessive heat and direct sun

WARNINGS

WARNINGS:For external use only. Do not use on damaged or broken skin. Stop use and ask a doctor if rash occurs. When using this product, keep out of eyes. Rinse with water to remove. Keep out of the reach of children. If swallowed, get medical help or contact a Poison Control Center right away.

Keep out of the reach of children.

DOSAGE AND ADMINISTRATION

Helps prevent sunburn. If used as directed with other sun protection measures (see directions), decreases the risk of skin cancer and early skin aging cuased by the sun.

Apply liberally 15 minutes befor sun exposure.

Principal Display Panel – 113 g Bottle Label

skin apeel

organic results • cruelty free

Pure Protect

SPF 40

Broad Spectrum

Water Resistant

(40 Mins)

Non-tinted . zinc oxide
antioxidants c + e

Net Wt. 4 oz/ 113 g

Graphic-Untitled